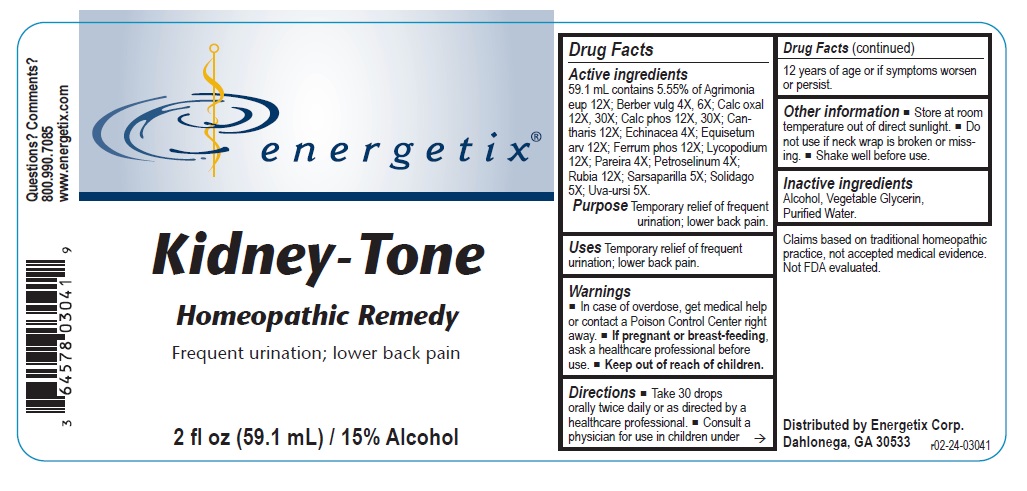 DRUG LABEL: Kidney-Tone
NDC: 64578-0149 | Form: LIQUID
Manufacturer: Energetix Corporation
Category: homeopathic | Type: HUMAN OTC DRUG LABEL
Date: 20241120

ACTIVE INGREDIENTS: AGRIMONIA EUPATORIA 12 [hp_X]/59.1 mL; BERBERIS VULGARIS ROOT BARK 4 [hp_X]/59.1 mL; CALCIUM OXALATE MONOHYDRATE 12 [hp_X]/59.1 mL; TRIBASIC CALCIUM PHOSPHATE 12 [hp_X]/59.1 mL; LYTTA VESICATORIA 12 [hp_X]/59.1 mL; ECHINACEA, UNSPECIFIED 4 [hp_X]/59.1 mL; EQUISETUM ARVENSE TOP 12 [hp_X]/59.1 mL; FERROSOFERRIC PHOSPHATE 12 [hp_X]/59.1 mL; LYCOPODIUM CLAVATUM SPORE 12 [hp_X]/59.1 mL; CHONDRODENDRON TOMENTOSUM ROOT 4 [hp_X]/59.1 mL; PETROSELINUM CRISPUM 4 [hp_X]/59.1 mL; RUBIA TINCTORUM ROOT 12 [hp_X]/59.1 mL; SARSAPARILLA 5 [hp_X]/59.1 mL; SOLIDAGO VIRGAUREA FLOWERING TOP 5 [hp_X]/59.1 mL; ARCTOSTAPHYLOS UVA-URSI LEAF 5 [hp_X]/59.1 mL
INACTIVE INGREDIENTS: ALCOHOL; GLYCERIN; WATER

Kidney-Tone

ACTIVE INGREDIENT

Active ingredients59.1 mL contains 5.55% of: Agrimonia eup 12X; Berberis vulg 4X, 6X; Calcarea oxal 12X, 30X; Calcarea phos 12X, 30X; Cantharis 12X; Echinacea 4X; Equisetum arv 12X; Ferrum phos 12X; Lycopodium 12X; Pareira 4X; Petroselinum 4X; Rubia 12X; Sarsaparilla 5X; Solidago 5X; Uva-ursi 5X.

Claims based on traditional homeopathic practice, not accepted medical evidence. Not FDA evaluated.

INDICATIONS AND USAGE

Uses Temporary relief of frequent urination; lower back pain.

Warnings

- In case of overdose, get medical help or contact a Poison Control Center right away.
- If pregnant or breast- feeding, ask a healthcare professional before use.

- Keep out of reach of children.

Directions

- Take 30 drops orally twice daily or as directed by a healthcare professional.
- Consult a physician for use in children under 12 years of age or if symptoms worsen or persist.

Other information

- Store at room temperature out of direct sunlight.
- Do not use if neck wrap is broken or missing.
- Shake well before use.

Inactive ingredientsAlcohol, Vegetable Glycerin, Purified Water.

QUESTIONS

Distributed by Energetix Corp.

Dahlonega, GA 30533

Questions? Comments?

800-990-7085

www.energetix.com

PACKAGE LABEL

energetix

Kidney-Tone

Homeopathic Remedy

Frequent urination; lower back pain

2 fl oz (59.1 mL) / 15% Alcohol

PURPOSE

Purpose Temporary relief of frequent urination; lower back pain.